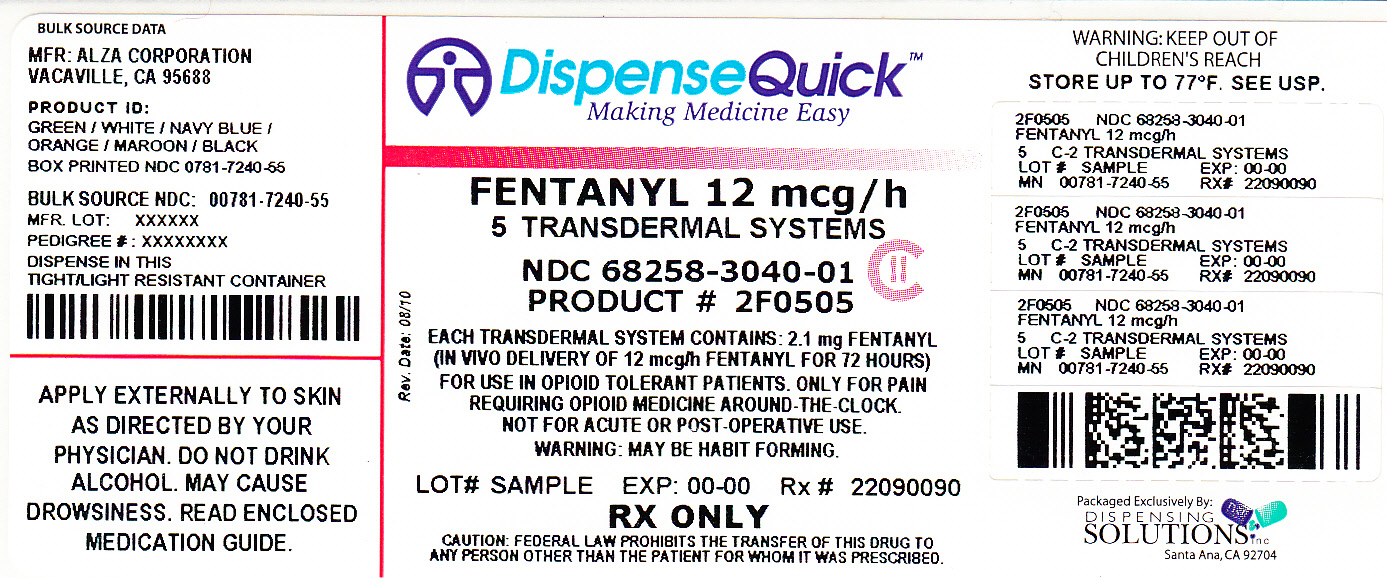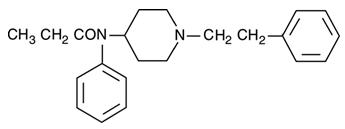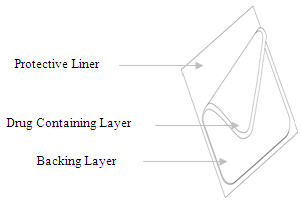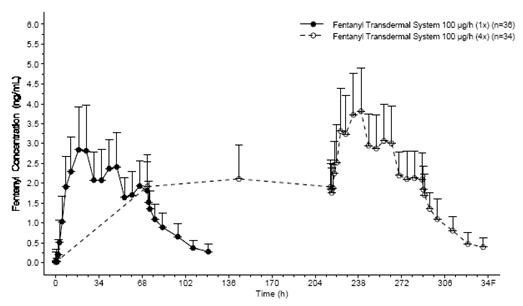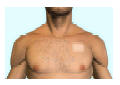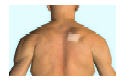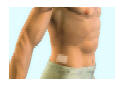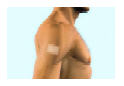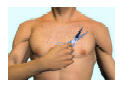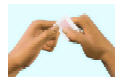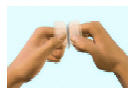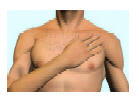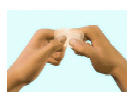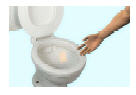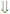 DRUG LABEL: Fentanyl
NDC: 68258-3040 | Form: PATCH
Manufacturer: Dispensing Solutions, Inc.
Category: prescription | Type: HUMAN PRESCRIPTION DRUG LABEL
Date: 20110901
DEA Schedule: CII

ACTIVE INGREDIENTS: Fentanyl 12 ug/1 1
INACTIVE INGREDIENTS: copovidone

FENTANYL TRANSDERMAL SYSTEM CII

Full Prescribing Information

FOR USE IN OPIOID-TOLERANT PATIENTS ONLY

BOXED WARNING

Fentanyl Transdermal System contains a high concentration of a potent Schedule II opioid agonist, fentanyl. Schedule II opioid substances which include fentanyl, hydromorphone, methadone, morphine, oxycodone, and oxymorphone have the highest potential for abuse and associated risk of fatal overdose due to respiratory depression. Fentanyl can be abused and is subject to criminal diversion. The high content of fentanyl in the patches (fentanyl transdermal system) may be a particular target for abuse and diversion.

Fentanyl transdermal system is indicated for management of persistent, moderate to severe chronic pain that:

- requires continuous, around-the-clock opioid administration for an extended period of time, and
- cannot be managed by other means such as non-steroidal analgesics, opioid combination products, or immediate-release opioids

Fentanyl transdermal system should ONLY be used in patients who are already receiving opioid therapy, who have demonstrated opioid tolerance, and who require a total daily dose at least equivalent to fentanyl transdermal system 25 mcg/h. Patients who are considered opioid-tolerant are those who have been taking, for a week or longer, at least 60 mg of morphine daily, or at least 30 mg of oral oxycodone daily, or at least 8 mg of oral hydromorphone daily or an equianalgesic dose of another opioid.

Because serious or life-threatening hypoventilation could occur, fentanyl transdermal system is contraindicated:

- in patients who are not opioid-tolerant
- in the management of acute pain or in patients who require opioid analgesia for a short period of time
- in the management of post-operative pain, including use after out-patient or day surgeries (e.g., tonsillectomies)
- in the management of mild pain
- in the management of intermittent pain (e.g., use on an as needed basis [prn])

(See CONTRAINDICATIONS for further information.)

Since the peak fentanyl concentrations generally occur between 20 and 72 hours of treatment, prescribers should be aware that serious or life threatening hypoventilation may occur, even in opioid-tolerant patients, during the initial application period.

The concomitant use of fentanyl transdermal system with all cytochrome P450 3A4 inhibitors (such as ritonavir, ketoconazole, itraconazole, troleandomycin, clarithromycin, nelfinavir, nefazodone, amiodarone, amprenavir, aprepitant, diltiazem, erythromycin, fluconazole, fosamprenavir, grapefruit juice, and verapamil) may result in an increase in fentanyl plasma concentrations, which could increase or prolong adverse drug effects and may cause potentially fatal respiratory depression. Patients receiving fentanyl transdermal system and any CYP3A4 inhibitor should be carefully monitored for an extended period of time and dosage adjustments should be made if warranted (see CLINICAL PHARMACOLOGY – Drug Interactions, WARNINGS, PRECAUTIONS, and DOSAGE AND ADMINISTRATION for further information).

The safety of fentanyl transdermal system has not been established in children under 2 years of age. Fentanyl transdermal system should be administered to children only if they are opioid-tolerant and 2 years of age or older (see PRECAUTIONS - Pediatric Use).

Fentanyl transdermal system is ONLY for use in patients who are already tolerant to opioid therapy of comparable potency. Use in non-opioid tolerant patients may lead to fatal respiratory depression. Overestimating the fentanyl transdermal system dose when converting patients from another opioid medication can result in fatal overdose with the first dose (see DOSAGE AND ADMINISTRATION – Initial Fentanyl Transdermal System Dose Selection). Due to the mean half-life of approximately 20–27 hours, patients who are thought to have had a serious adverse event, including overdose, will require monitoring and treatment for at least 24 hours.

Fentanyl transdermal system can be abused in a manner similar to other opioid agonists, legal or illicit. This risk should be considered when administering, prescribing, or dispensing fentanyl transdermal system in situations where the healthcare professional is concerned about increased risk of misuse, abuse, or diversion.

Persons at increased risk for opioid abuse include those with a personal or family history of substance abuse (including drug or alcohol abuse or addiction) or mental illness (e.g., major depression). Patients should be assessed for their clinical risks for opioid abuse or addiction prior to being prescribed opioids. All patients receiving opioids should be routinely monitored for signs of misuse, abuse, and addiction. Patients at increased risk of opioid abuse may still be appropriately treated with modified-release opioid formulations; however, these patients will require intensive monitoring for signs of misuse, abuse, or addiction.

Fentanyl transdermal system patches are intended for transdermal use (on intact skin) only. Do not use a fentanyl transdermal system patch if the pouch seal is broken or the patch is cut, damaged, or changed in any way.

Avoid exposing the fentanyl transdermal system application site and surrounding area to direct external heat sources, such as heating pads or electric blankets, heat or tanning lamps, saunas, hot tubs, and heated water beds, while wearing the system. Avoid taking hot baths or sunbathing. There is a potential for temperature-dependent increases in fentanyl released from the system resulting in possible overdose and death. Patients wearing fentanyl transdermal systems who develop fever or increased core body temperature due to strenuous exertion should be monitored for opioid side effects and the fentanyl transdermal system dose should be adjusted if necessary.

DESCRIPTION

Fentanyl transdermal system is a transdermal system providing continuous systemic delivery of fentanyl, a potent opioid analgesic, for 72 hours. The chemical name is N-Phenyl-N-(1-(2-phenylethyl)-4-piperidinyl) propanamide. The structural formula is:

The molecular weight of fentanyl base is 336.5, and the empirical formula is C22H28N2O. The n-octanol:water partition coefficient is 860:1. The pKa is 8.4.

System Components and Structure

The amount of fentanyl released from each system per hour is proportional to the surface area (25 mcg/h per 10.5 cm^2). The composition per unit area of all system sizes is identical.

Dose [Nominal delivery rate per hour] (mcg/h) | Size (cm^2) | Fentanyl Content (mg)
12 [Nominal delivery rate is 12.5 mcg/hr] | 5.25 | 2.1
25 | 10.5 | 4.2
50 | 21 | 8.4
75 | 31.5 | 12.6
100 | 42 | 16.8

Fentanyl transdermal system is a rectangular transparent unit comprising a protective liner and two functional layers. Proceeding from the outer surface toward the surface adhering to skin, these layers are:

1) a backing layer of polyester/ethyl vinyl acetate film; 2) a drug-in-adhesive layer. Before use, a protective liner covering the adhesive layer is removed and discarded.

The active component of the system is fentanyl. The remaining components are pharmacologically inactive.

CLINICAL PHARMACOLOGY

Pharmacology

Fentanyl is an opioid analgesic. Fentanyl interacts predominately with the opioid mu-receptor. These mu-binding sites are discretely distributed in the human brain, spinal cord, and other tissues. In clinical settings, fentanyl exerts its principal pharmacologic effects on the central nervous system.

In addition to analgesia, alterations in mood, euphoria, dysphoria, and drowsiness commonly occur. Fentanyl depresses the respiratory centers, depresses the cough reflex, and constricts the pupils. Analgesic blood concentrations of fentanyl may cause nausea and vomiting directly by stimulating the chemoreceptor trigger zone, but nausea and vomiting are significantly more common in ambulatory than in recumbent patients, as is postural syncope.

Opioids increase the tone and decrease the propulsive contractions of the smooth muscle of the gastrointestinal tract. The resultant prolongation in gastrointestinal transit time may be responsible for the constipating effect of fentanyl. Because opioids may increase biliary tract pressure, some patients with biliary colic may experience worsening rather than relief of pain.

While opioids generally increase the tone of urinary tract smooth muscle, the net effect tends to be variable, in some cases producing urinary urgency, in others, difficulty in urination. At therapeutic dosages, fentanyl usually does not exert major effects on the cardiovascular system. However, some patients may exhibit orthostatic hypotension and fainting.

Histamine assays and skin wheal testing in clinical studies indicate that clinically significant histamine release rarely occurs with fentanyl administration. Clinical assays show no clinically significant histamine release in dosages up to 50 mcg/kg.

Pharmacokinetics

(see graph and tables)

The fentanyl transdermal system is a drug-in-adhesive matrix designed formulation. Fentanyl is released from the matrix at a nearly constant amount per unit time. The concentration gradient existing between the matrix and the lower concentration in the skin drives drug release. Fentanyl moves in the direction of the lower concentration at a rate determined by the matrix and the diffusion of fentanyl through the skin layers. While the actual rate of fentanyl delivery to the skin varies over the 72-hour application period, each system is labeled with a nominal flux which represents the average amount of drug delivered to the systemic circulation per hour across average skin.

While there is variation in dose delivered among patients, the nominal flux of the systems (12.5, 25, 50, 75, and 100 mcg of fentanyl per hour) is sufficiently accurate as to allow individual titration of dosage for a given patient.

Following fentanyl transdermal system application, the skin under the system absorbs fentanyl, and a depot of fentanyl concentrates in the upper skin layers. Fentanyl then becomes available to the systemic circulation. Serum fentanyl concentrations increase gradually following initial fentanyl transdermal system application, generally leveling off between 12 and 24 hours and remaining relatively constant, with some fluctuation, for the remainder of the 72-hour application period. Peak serum concentrations of fentanyl generally occurred between 20 and 72 hours after initial application (see Table A). Serum fentanyl concentrations achieved are proportional to the fentanyl transdermal system delivery rate. With continuous use, serum fentanyl concentrations continue to rise for the first two system applications. By the end of the second 72-hour application, a steady-state serum concentration is reached and is maintained during subsequent applications of a patch of the same size. Patients reach and maintain a steady-state serum concentration that is determined by individual variation in skin permeability and body clearance of fentanyl.

After system removal, serum fentanyl concentrations decline gradually, falling about 50% in approximately 20–27 hours. Continued absorption of fentanyl from the skin accounts for a slower disappearance of the drug from the serum than is seen after an IV infusion, where the apparent half-life is approximately 7 (range 3–12) hours.

Serum Fentanyl Concentrations Following Single and Multiple Applications of Fentanyl Transdermal System 100 mcg/h

TABLE A: FENTANYL PHARMACOKINETIC PARAMETERS FOLLOWING FIRST 72-HOUR APPLICATION OF FENTANYL TRANSDERMAL SYSTEM
 | Mean (SD) Time to Maximal Concentration Tmax (h) | Mean (SD) Maximal Concentration Cmax (ng/mL)
Fentanyl Transdermal System 12 mcg/h | 28.8 (13.7) | 0.38 (0.13) [Cmax values dose normalized from 4 × 12.5 mcg/h]
Fentanyl Transdermal System 25 mcg/h | 31.7 (16.5) | 0.85 (0.26)
Fentanyl Transdermal System 50 mcg/h | 32.8 (15.6) | 1.72 (0.53)
Fentanyl Transdermal System 75 mcg/h | 35.8 (14.1) | 2.32 (0.86)
Fentanyl Transdermal System 100 mcg/h | 29.9 (13.3) | 3.36 (1.28)
NOTE: After system removal there is continued systemic absorption from residual fentanyl in the skin so that serum concentrations fall 50%, on average, in approximately 20–27 hours.

TABLE B: RANGE OF PHARMACOKINETIC PARAMETERS OF INTRAVENOUS FENTANYL IN PATIENTS
 | Clearance (L/h) Range [70 kg] | Volume of Distribution VSS (L/kg) Range | Half-Life t1/2 (h) Range
Surgical Patients | 27 – 75 | 3 – 8 | 3 – 12
Hepatically Impaired Patients | 3 – 80 [Estimated] | 0.8 – 8 | 4 – 12
Renally Impaired Patients | 30 – 78 | – | –
NOTE: Information on volume of distribution and half-life not available for renally impaired patients.

Fentanyl plasma protein binding capacity decreases with increasing ionization of the drug. Alterations in pH may affect its distribution between plasma and the central nervous system. Fentanyl accumulates in the skeletal muscle and fat and is released slowly into the blood. The average volume of distribution for fentanyl is 6 L/kg (range 3–8; N=8).

Fentanyl is metabolized primarily via human cytochrome P450 3A4 isoenzyme system. In humans, the drug appears to be metabolized primarily by oxidative N-dealkylation to norfentanyl and other inactive metabolites that do not contribute materially to the observed activity of the drug. Within 72 hours of IV fentanyl administration, approximately 75% of the dose is excreted in urine, mostly as metabolites with less than 10% representing unchanged drug. Approximately 9% of the dose is recovered in the feces, primarily as metabolites. Mean values for unbound fractions of fentanyl in plasma are estimated to be between 13 and 21%.

Skin does not appear to metabolize fentanyl delivered transdermally. This was determined in a human keratinocyte cell assay and in clinical studies in which 92% of the dose delivered from the system was accounted for as unchanged fentanyl that appeared in the systemic circulation.

Special Populations

Hepatic or Renal Disease

Insufficient information exists to make recommendations regarding the use of fentanyl transdermal system in patients with impaired renal or hepatic function. Fentanyl is metabolized primarily via human cytochrome P450 3A4 isoenzyme system and mostly eliminated in urine. If the drug is used in these patients, it should be used with caution because of the hepatic metabolism and renal excretion of fentanyl.

Pediatric Use

In 1.5 to 5 year old, non-opioid-tolerant pediatric patients, the fentanyl plasma concentrations were approximately twice as high as that of adult patients. In older pediatric patients, the pharmacokinetic parameters were similar to that of adults. However, these findings have been taken into consideration in determining the dosing recommendations for opioid-tolerant pediatric patients (2 years of age and older). For pediatric dosing information, refer to DOSAGE AND ADMINISTRATION section.

Geriatric Use

Data from intravenous studies with fentanyl suggest that the elderly patients may have reduced clearance and a prolonged half-life. Moreover elderly patients may be more sensitive to the active substance than younger patients. A study conducted with the patch in elderly patients demonstrated that fentanyl pharmacokinetics did not differ significantly from young adult subjects, although peak serum concentrations tended to be lower and mean half-life values were prolonged to approximately 34 hours.

Respiratory depression is the chief hazard in elderly or debilitated patients, usually following large initial doses in non-tolerant patients or when opioids are given in conjunction with other agents that depress respiration.

Fentanyl transdermal system should be used with caution in elderly, cachectic or debilitated patients as they may have altered pharmacokinetics due to poor fat stores, muscle wasting, or altered clearance (see DOSAGE AND ADMINISTRATION).

Drug Interactions

The interaction between ritonavir, a CPY3A4 inhibitor, and fentanyl was investigated in eleven healthy volunteers in a randomized crossover study. Subjects received oral ritonavir or placebo for 3 days. The ritonavir dose was 200 mg tid on Day 1 and 300 mg tid on Day 2 followed by one morning dose of 300 mg on Day 3. On Day 2, fentanyl was given as a single IV dose at 5 mcg/kg two hours after the afternoon dose of oral ritonavir or placebo. Naloxone was administered to counteract the side effects of fentanyl. The results suggested that ritonavir might decrease the clearance of fentanyl by 67%, resulting in a 174% (range 52%–420%) increase in fentanyl AUC0–∞. Coadministration of ritonavir in patients receiving fentanyl transdermal system has not been studied; however, an increase in fentanyl AUC is expected (see BOX WARNING, WARNINGS, PRECAUTIONS, and DOSAGE AND ADMINISTRATION).

Fentanyl is metabolized mainly via the human cytochrome P450 3A4 isoenzyme system (CYP3A4), therefore, potential interactions may occur when fentanyl transdermal system is given concurrently with agents that affect CYP3A4 activity. Coadminstration with agents that induce CYP3A4 activity may reduce the efficacy of fentanyl transdermal system. The concomitant use of transdermal fentanyl with all CYP3A4 inhibitors (such as ritonavir, ketoconazole, itraconazole, troleandomycin, clarithromycin, nelfinavir, nefazadone, amiodarone, amprenavir, aprepitant, diltiazem, erythromycin, fluconazole, fosamprenavir, grapefruit juice, and verapamil) may result in an increase in fentanyl plasma concentrations, which could increase or prolong adverse drug effects and may cause potentially fatal respiratory depression. Patients receiving fentanyl transdermal system and any CYP3A4 inhibitor should be carefully monitored for an extended period of time and dosage adjustments should be made if warranted (see BOX WARNING, WARNINGS, PRECAUTIONS, and DOSAGE AND ADMINISTRATION for further information).

PHARMACODYNAMICS

Ventilatory Effects

Because of the risk for serious or life-threatening hypoventilation, fentanyl transdermal system is CONTRAINDICATED in the treatment of post-operative and acute pain and in patients who are not opioid-tolerant. In clinical trials of 357 patients with acute pain treated with fentanyl transdermal system, 13 patients experienced hypoventilation. Hypoventilation was manifested by respiratory rates of less than 8 breaths/minute or a pCO2 greater than 55 mm Hg. In these studies, the incidence of hypoventilation was higher in nontolerant women (10) than in men (3) and in patients weighing less than 63 kg (9 of 13). Although patients with impaired respiration were not common in the trials, they had higher rates of hypoventilation. In addition, post-marketing reports have been received that describe opioid-naive post-operative patients who have experienced clinically significant hypoventilation and death with fentanyl transdermal system.

While most adult and pediatric patients using fentanyl transdermal system chronically develop tolerance to fentanyl induced hypoventilation, episodes of slowed respirations may occur at any time during therapy.

Hypoventilation can occur throughout the therapeutic range of fentanyl serum concentrations, especially for patients who have an underlying pulmonary condition or who receive usual doses of opioids or other CNS drugs associated with hypoventilation in addition to fentanyl transdermal system. The use of fentanyl transdermal system is contraindicated in patients who are not tolerant to opioid therapy.

The use of fentanyl transdermal system should be monitored by clinical evaluation, especially within the initial 24–72 hours when serum concentrations from the initial patch will peak, and following increases in dosage. Fentanyl transdermal system should be administered to children only if they are opioid-tolerant and 2 years of age or older.

See BOX WARNING, CONTRAINDICATIONS, WARNINGS, PRECAUTIONS, ADVERSE REACTIONS, and OVERDOSAGE for additional information on hypoventilation.

Cardiovascular Effects

Fentanyl may infrequently produce bradycardia. The incidence of bradycardia in clinical trials with fentanyl transdermal system was less than 1%.

CNS Effects

Central nervous system effects increase with increasing serum fentanyl concentrations.

INDICATIONS AND USAGE

Fentanyl transdermal system is indicated for management of persistent, moderate to severe chronic pain that:

- requires continuous, around-the-clock opioid administration for an extended period of time, and
- cannot be managed by other means such as non-steroidal analgesics, opioid combination products, or immediate-release opioids.

Fentanyl transdermal system should ONLY be used in patients who are already receiving opioid therapy, who have demonstrated opioid tolerance, and who require a total daily dose at least equivalent to fentanyl transdermal system 25 mcg/h (see DOSAGE AND ADMINISTRATION). Patients who are considered opioid-tolerant are those who have been taking, for a week or longer, at least 60 mg of morphine daily, or at least 30 mg of oral oxycodone daily, or at least 8 mg of oral hydromorphone daily, or an equianalgesic dose of another opioid.

Because serious or life-threatening hypoventilation could result, fentanyl transdermal system is contraindicated for use on an as needed basis (i.e., prn), for the management of post-operative or acute pain, or in patients who are not opioid-tolerant or who require opioid analgesia for a short period of time (see BOX WARNING and CONTRAINDICATIONS).

An evaluation of the appropriateness and adequacy of treating with immediate-release opioids is advisable prior to initiating therapy with any modified-release opioid. Prescribers should individualize treatment in every case, initiating therapy at the appropriate point along a progression from non-opioid analgesics, such as non-steroidal anti-inflammatory drugs and acetaminophen, to opioids, in a plan of pain management such as outlined by the World Health Organization, the Agency for Health Research and Quality, the Federation of State Medical Boards Model Policy, or the American Pain Society.

Patients should be assessed for their clinical risks for opioid abuse or addiction prior to being prescribed opioids. Patients receiving opioids should be routinely monitored for signs of misuse, abuse, and addiction. Persons at increased risk for opioid abuse include those with a personal or family history of substance abuse (including drug or alcohol abuse or addiction) or mental illness (e.g., major depression). Patients at increased risk may still be appropriately treated with modified-release opioid formulations; however these patients will require intensive monitoring for signs of misuse, abuse, or addiction.

CONTRAINDICATIONS

Because serious or life-threatening hypoventilation could occur, fentanyl transdermal system is contraindicated:

- in patients who are not opioid-tolerant
- in the management of acute pain or in patients who require opioid analgesia for a short period of time
- in the management of post-operative pain, including use after out-patient or day surgeries, (e.g., tonsillectomies)
- in the management of mild pain
- in the management of intermittent pain (e.g., use on an as needed basis [prn])
- in situations of significant respiratory depression, especially in unmonitored settings where there is a lack of resuscitative equipment
- in patients who have acute or severe bronchial asthma

Fentanyl transdermal system is contraindicated in patients who have or are suspected of having paralytic ileus.

Fentanyl transdermal system is contraindicated in patients with known hypersensitivity to fentanyl or any components of this product.

WARNINGS

Fentanyl transdermal system patches are intended for transdermal use (on intact skin) only. Do not use a fentanyl transdermal system patch if the pouch seal is broken or the patch is cut, damaged, or changed in any way.

The safety of fentanyl transdermal system has not been established in children under 2 years of age. Fentanyl transdermal system should be administered to children only if they are opioid-tolerant and 2 years of age or older (see PRECAUTIONS – Pediatric Use).

Fentanyl transdermal system is ONLY for use in patients who are already tolerant to opioid therapy of comparable potency. Use in non-opioid tolerant patients may lead to fatal respiratory depression. Overestimating the fentanyl transdermal system dose when converting patients from another opioid medication can result in fatal overdose with the first dose. The mean half-life is approximately 20–27 hours. Therefore, patients who have experienced serious adverse events, including overdose, will require monitoring for at least 24 hours after fentanyl transdermal system removal since serum fentanyl concentrations decline gradually and reach an approximate 50% reduction in serum concentrations 20–27 hours after system removal.

Fentanyl transdermal system should be prescribed only by persons knowledgeable in the continuous administration of potent opioids, in the management of patients receiving potent opioids for treatment of pain, and in the detection and management of hypoventilation including the use of opioid antagonists.

All patients and their caregivers should be advised to avoid exposing the fentanyl transdermal system application site and surrounding area to direct external heat sources, such as heating pads or electric blankets, heat or tanning lamps, saunas, hot tubs, and heated water beds, etc., while wearing the system. Patients should be advised against taking hot baths or sunbathing. There is a potential for temperature-dependent increases in fentanyl released from the system resulting in possible overdose and death. A clinical pharmacology trial conducted in healthy adult subjects has shown that the application of heat over the fentanyl transdermal system increased mean fentanyl AUC values by 120% and mean Cmax values by 61%.

Based on a pharmacokinetic model, serum fentanyl concentrations could theoretically increase by approximately one-third for patients with a body temperature of 40°C (104°F) due to temperature-dependent increases in fentanyl released from the system and increased skin permeability. Patients wearing fentanyl transdermal systems who develop fever or increased core body temperature due to strenuous exertion should be monitored for opioid side effects and the fentanyl transdermal system dose should be adjusted if necessary.

Death and other serious medical problems have occurred when people were accidentally exposed to fentanyl transdermal system. Examples of accidental exposure include transfer of a fentanyl transdermal system patch from an adult's body to a child while hugging, accidental sitting on a patch and possible accidental exposure of a caregiver's skin to the medication in the patch while the caregiver was applying or removing the patch.

Placing fentanyl transdermal system in the mouth, chewing it, swallowing it, or using it in ways other than indicated may cause choking or overdose that could result in death.

Misuse, Abuse and Diversion of Opioids

Fentanyl is an opioid agonist of the morphine-type. Such drugs are sought by drug abusers and people with addiction disorders and are subject to criminal diversion.

Fentanyl can be abused in a manner similar to other opioids, legal or illicit. This should be considered when prescribing or dispensing fentanyl transdermal system in situations where the physician or pharmacist is concerned about an increased risk of misuse, abuse, or diversion.

Fentanyl transdermal system has been reported as being abused by other methods and routes of administration. These practices will result in uncontrolled delivery of the opioid and pose a significant risk to the abuser that could result in overdose and death (see WARNINGS and DRUG ABUSE AND ADDICTION).

Concerns about abuse, addiction, and diversion should not prevent the proper management of pain. However, all patients treated with opioids require careful monitoring for signs of abuse and addiction, since use of opioid analgesic products carries the risk of addiction even under appropriate medical use.

Healthcare professionals should contact their state professional licensing board or state controlled substances authority for information on how to prevent and detect abuse or diversion of this product.

Hypoventilation (Respiratory Depression)

Serious or life-threatening hypoventilation may occur at any time during the use of fentanyl transdermal system especially during the initial 24–72 hours following initiation of therapy and following increases in dose.

Because significant amounts of fentanyl continue to be absorbed from the skin for 20‑27 hours or more after the patch is removed, hypoventilation may persist beyond the removal of fentanyl transdermal system. Consequently, patients with hypoventilation should be carefully observed for degree of sedation and their respiratory rate monitored until respiration has stabilized.

The use of concomitant CNS active drugs requires special patient care and observation.

Respiratory depression is the chief hazard of opioid agonists, including fentanyl the active ingredient in fentanyl transdermal system. Respiratory depression is more likely to occur in elderly or debilitated patients, usually following large initial doses in non-tolerant patients, or when opioids are given in conjunction with other drugs that depress respiration.

Respiratory depression from opioids is manifested by a reduced urge to breathe and a decreased rate of respiration, often associated with the "sighing" pattern of breathing (deep breaths separated by abnormally long pauses). Carbon dioxide retention from opioid-induced respiratory depression can exacerbate the sedating effects of opioids. This makes overdoses involving drugs with sedative properties and opioids especially dangerous.

Fentanyl transdermal system should be used with extreme caution in patients with significant chronic obstructive pulmonary disease or cor pulmonale, and in patients having a substantially decreased respiratory reserve, hypoxia, hypercapnia, or pre-existing respiratory depression. In such patients, even usual therapeutic doses of fentanyl transdermal system may decrease respiratory drive to the point of apnea. In these patients, alternative non-opioid analgesics should be considered, and opioids should be employed only under careful medical supervision at the lowest effective dose.

Chronic Pulmonary Disease

Because potent opioids can cause serious or life-threatening hypoventilation, fentanyl transdermal system should be administered with caution to patients with pre-existing medical conditions predisposing them to hypoventilation. In such patients, normal analgesic doses of opioids may further decrease respiratory drive to the point of respiratory failure.

Head Injuries and Increased Intracranial Pressure

Fentanyl transdermal system should not be used in patients who may be particularly susceptible to the intracranial effects of CO2 retention such as those with evidence of increased intracranial pressure, impaired consciousness, or coma. Opioids may obscure the clinical course of patients with head injury. Fentanyl transdermal system should be used with caution in patients with brain tumors.

Interactions with Other CNS Depressants

The concomitant use of fentanyl transdermal system with other central nervous system depressants, including but not limited to other opioids, sedatives, hypnotics, tranquilizers (e.g., benzodiazepines), general anesthetics, phenothiazines, skeletal muscle relaxants, and alcohol, may cause respiratory depression, hypotension, and profound sedation or potentially result in coma. When such combined therapy is contemplated, the dose of one or both agents should be significantly reduced.

Interactions with Alcohol and Drugs of Abuse

Fentanyl may be expected to have additive CNS depressant effects when used in conjunction with alcohol, other opioids, or illicit drugs that cause central nervous system depression.

Interactions with CYP3A4 Inhibitors

The concomitant use of transdermal fentanyl with all CYP3A4 inhibitors (such as ritonavir, ketoconazole, itraconazole, troleandomycin, clarithromycin, nelfinavir, nefazadone, amiodarone, amprenavir, aprepitant, diltiazem, erythromycin, fluconazole, fosamprenavir, grapefruit juice, and verapamil) may result in an increase in fentanyl plasma concentrations, which could increase or prolong adverse drug effects and may cause potentially fatal respiratory depression. Patients receiving fentanyl transdermal system and any CYP3A4 inhibitor should be carefully monitored for an extended period of time, and dosage adjustments should be made if warranted (see BOX WARNING, CLINICAL PHARMACOLOGY – Drug Interactions, PRECAUTIONS, and DOSAGE AND ADMINISTRATION for further information).

PRECAUTIONS

General

Fentanyl transdermal system should not be used to initiate opioid therapy in patients who are not opioid-tolerant. Children converting to fentanyl transdermal system should be opioid-tolerant and 2 years of age or older (see BOX WARNING).

Patients, family members, and caregivers should be instructed to keep patches (new and used) out of the reach of children and others for whom fentanyl transdermal system was not prescribed. A considerable amount of active fentanyl remains in fentanyl transdermal system even after use as directed. Accidental or deliberate application or ingestion by a child or adolescent will cause respiratory depression that could result in death.

Cardiac Disease

Fentanyl may produce bradycardia. Fentanyl should be administered with caution to patients with bradyarrhythmias.

Hepatic or Renal Disease

Insufficient information exists to make recommendations regarding the use of fentanyl transdermal system in patients with impaired renal or hepatic function. If the drug is used in these patients, it should be used with caution because of the hepatic metabolism and renal excretion of fentanyl.

Use in Pancreatic/Biliary Tract Disease

Fentanyl transdermal system may cause spasm of the sphincter of Oddi and should be used with caution in patients with biliary tract disease, including acute pancreatitis. Opioids like fentanyl transdermal system may cause increases in the serum amylase concentration.

Tolerance

Tolerance is a state of adaptation in which exposure to a drug induces changes that result in a diminution of one or more of the drug's effects over time. Tolerance may occur to both the desired and undesired effects of drugs, and may develop at different rates for different effects.

Physical Dependence

Physical dependence is a state of adaptation that is manifested by an opioid specific withdrawal syndrome that can be produced by abrupt cessation, rapid dose reduction, decreasing blood concentration of the drug, and/or administration of an antagonist. The opioid abstinence or withdrawal syndrome is characterized by some or all of the following: restlessness, lacrimation, rhinorrhea, yawning, perspiration, chills, piloerection, myalgia, mydriasis, irritability, anxiety, backache, joint pain, weakness, abdominal cramps, insomnia, nausea, anorexia, vomiting, diarrhea, or increased blood pressure, respiratory rate, or heart rate. In general, opioids should not be abruptly discontinued (see DOSAGE AND ADMINISTRATION – Discontinuation of Fentanyl Transdermal System).

Ambulatory Patients

Strong opioid analgesics impair the mental or physical abilities required for the performance of potentially dangerous tasks, such as driving a car or operating machinery. Patients who have been given fentanyl transdermal system should not drive or operate dangerous machinery unless they are tolerant to the effects of the drug.

Information for Patients

Patients and their caregivers should be provided with a Medication Guide each time fentanyl transdermal system is dispensed because new information may be available.

Patients receiving fentanyl transdermal system patches should be given the following instructions by the physician:

1. Patients should be advised that fentanyl transdermal system patches contain fentanyl, an opioid pain medicine similar to morphine, hydromorphone, methadone, oxycodone, and oxymorphone.
2. Patients should be advised that each fentanyl transdermal system patch may be worn continuously for 72 hours, and that each patch should be applied to a different skin site after removal of the previous transdermal patch.
3. Patients should be advised that fentanyl transdermal system patches should be applied to intact, non-irritated, and non-irradiated skin on a flat surface such as the chest, back, flank, or upper arm. Additionally, patients should be advised of the following:
  - In young children or persons with cognitive impairment, the patch should be put on the upper back to lower the chances that the patch will be removed and placed in the mouth.
  - Hair at the application site should be clipped (not shaved) prior to patch application.
  - If the site of fentanyl transdermal system application must be cleansed prior to application of the patch, do so with clear water.
  - Do not use soaps, oils, lotions, alcohol, or any other agents that might irritate the skin or alter its characteristics.
  - Allow the skin to dry completely prior to patch application.
4. Patients should be advised that fentanyl transdermal system should be applied immediately upon removal from the sealed pouch and after removal of the protective liner. Additionally the patient should be advised of the following:
  - The fentanyl transdermal system patch should not be used if the pouch seal is broken, or if the patch is cut, damaged, or changed in any way.
  - The transdermal patch should be pressed firmly in place with the palm of the hand for 30 seconds, making sure the contact is complete, especially around the edges.
  - The patch should not be folded so that only part of the patch is exposed.
5. Patients should be advised that the dose of fentanyl transdermal system or the number of patches applied to the skin should NEVER be adjusted without the prescribing healthcare professional's instruction.
6. Patients should be advised that while wearing the patch, they should avoid exposing the fentanyl transdermal system application site and surrounding area to direct external heat sources, such as:
  - heating pads,
  - electric blankets,
  - sunbathing,
  - heat or tanning lamps,
  - saunas,
  - hot tubs or hot baths, and
  - heated water beds, etc.
7. Patients should also be advised of a potential for temperature-dependent increases in fentanyl release from the patch that could result in an overdose of fentanyl; therefore, patients who develop a high fever or increased body temperature due to strenuous exertion while wearing the patch should contact their physician.
8. Patients should be advised that if they experience problems with adhesion of the fentanyl transdermal system patch, they may tape the edges of the patch with first aid tape. If problems with adhesion persist, patients may overlay the patch with a transparent adhesive film dressing (e.g., BioclusiveTM or TegadermTM).
9. Patients should be advised that if the patch falls off before 72 hours a new patch may be applied to a different skin site.
10. Patients should be advised to fold (so that the adhesive side adheres to itself) and immediately flush down the toilet used fentanyl transdermal system patches after removal from the skin.
11. Patients should be advised that fentanyl transdermal system may impair mental and/or physical ability required for the performance of potentially hazardous tasks (e.g., driving, operating machinery).
12. Patients should be advised to refrain from any potentially dangerous activity when starting on fentanyl transdermal system or when their dose is being adjusted, until it is established that they have not been adversely affected.
13. Patients should be advised that fentanyl transdermal system should not be combined with alcohol or other CNS depressants (e.g. sleep medications, tranquilizers) because dangerous additive effects may occur, resulting in serious injury or death.
14. Patients should be advised to consult their physician or pharmacist if other medications are being or will be used with fentanyl transdermal system.
15. Patients should be advised of the potential for severe constipation.
16. Patients should be advised that if they have been receiving treatment with fentanyl transdermal system and cessation of therapy is indicated, it may be appropriate to taper the fentanyl transdermal system dose, rather than abruptly discontinue it, due to the risk of precipitating withdrawal symptoms.
17. Patients should be advised that fentanyl transdermal system contains fentanyl, a drug with high potential for abuse.
18. Patients, family members, and caregivers should be advised to protect fentanyl transdermal system from theft or misuse in the work or home environment.
19. Patients should be instructed to keep fentanyl transdermal system in a secure place out of the reach of children due to the high risk of fatal respiratory depression.
20. Patients should be advised that fentanyl transdermal system should never be given to anyone other than the individual for whom it was prescribed because of the risk of death or other serious medical problems to that person for whom it was not intended.
21. Patients should be informed that, if the patch dislodges and accidentally sticks to the skin of another person, they should immediately take the patch off, wash the exposed area with water and seek medical attention for the accidentally exposed individual.
22. When fentanyl transdermal system is no longer needed, the unused patches should be removed from their pouches, folded so that the adhesive side of the patch adheres to itself, and flushed down the toilet.
23. Women of childbearing potential who become, or are planning to become pregnant, should be advised to consult a physician prior to initiating or continuing therapy with fentanyl transdermal system.
24. Patients should be informed that accidental exposure or misuse may lead to death or other serious medical problems.

Drug Interactions

Agents Affecting Cytochrome P450 3A4 Isoenzyme System

Fentanyl is metabolized mainly via the human cytochrome P450 3A4 isoenzyme system (CYP3A4), therefore potential interactions may occur when fentanyl transdermal system is given concurrently with agents that affect CYP3A4 activity. Coadminstration with agents that induce CYP3A4 activity may reduce the efficacy of fentanyl transdermal system. The concomitant use of transdermal fentanyl with all CYP3A4 inhibitors (such as ritonavir, ketoconazole, itraconazole, troleandomycin, clarithromycin, nelfanivir, nefazadone, amiodarone, amprenavir, aprepitant, diltiazem, erythromycin, fluconazole, fosamprenavir, grapefruit juice, and verapamil) may result in an increase in fentanyl plasma concentrations, which could increase or prolong adverse drug effects and may cause fatal respiratory depression. Patients receiving fentanyl transdermal system and any CYP3A4 inhibitor should be carefully monitored for an extended period of time, and dosage adjustments should be made if warranted (see BOX WARNING, CLINICAL PHARMACOLOGY – Drug Interactions, WARNINGS, and DOSAGE AND ADMINISTRATION for further information).

Central Nervous System Depressants

The concomitant use of fentanyl transdermal system with other central nervous system depressants, including but not limited to other opioids, sedatives, hypnotics, tranquilizers (e.g., benzodiazepines), general anesthetics, phenothiazines, skeletal muscle relaxants, and alcohol, may cause respiratory depression, hypotension, and profound sedation, or potentially result in coma or death. When such combined therapy is contemplated, the dose of one or both agents should be significantly reduced.

MAO Inhibitors

Fentanyl transdermal system is not recommended for use in patients who have received MAOI within 14 days because severe and unpredictable potentiation by MAO inhibitors has been reported with opioid analgesics.

Carcinogenesis, Mutagenesis, and Impairment of Fertility

In a two-year carcinogenicity study conducted in rats, fentanyl was not associated with an increased incidence of tumors at subcutaneous doses up to 33 µg/kg/day in males or 100 µg/kg/day in females (0.16 and 0.39 times the human daily exposure obtained via the 100 mcg/h patch based on AUC0–24h comparison). There was no evidence of mutagenicity in the Ames Salmonella mutagenicity assay, the primary rat hepatocyte unscheduled DNA synthesis assay, the BALB/c 3T3 transformation test, and the human lymphocyte and CHO chromosomal aberration in-vitro assays.

The potential effects of fentanyl on male and female fertility were examined in the rat model via two separate experiments. In the male fertility study, male rats were treated with fentanyl (0, 0.025, 0.1 or 0.4 mg/kg/day) via continuous intravenous infusion for 28 days prior to mating; female rats were not treated. In the female fertility study, female rats were treated with fentanyl (0, 0.025, 0.1 or 0.4 mg/kg/day) via continuous intravenous infusion for 14 days prior to mating until day 16 of pregnancy; male rats were not treated. Analysis of fertility parameters in both studies indicated that an intravenous dose of fentanyl up to 0.4 mg/kg/day to either the male or the female alone produced no effects on fertility (this dose is approximately 1.6 times the daily human dose administered by a 100 mcg/hr patch on a mg/m^2 basis). In a separate study, a single daily bolus dose of fentanyl was shown to impair fertility in rats when given in intravenous doses of 0.3 times the human dose for a period of 12 days.

Pregnancy

Pregnancy Category C

No epidemiological studies of congenital anomalies in infants born to women treated with fentanyl during pregnancy have been reported.

The potential effects of fentanyl on embryo-fetal development were studied in the rat, mouse, and rabbit models. Published literature reports that administration of fentanyl (0, 10, 100, or 500 µg/kg/day) to pregnant female Sprague-Dawley rats from day 7 to 21 via implanted microosmotic minipumps did not produce any evidence of teratogenicity (the high dose is approximately 2 times the daily human dose administered by a 100 mcg/hr patch on a mg/m^2 basis). In contrast, the intravenous administration of fentanyl (0, 0.01, or 0.03 mg/kg) to bred female rats from gestation day 6 to 18 suggested evidence of embryotoxicity and a slight increase in mean delivery time in the 0.03 mg/kg/day group. There was no clear evidence of teratogenicity noted.

Pregnant female New Zealand White rabbits were treated with fentanyl (0, 0.025, 0.1, 0.4 mg/kg) via intravenous infusion from day 6 to day 18 of pregnancy. Fentanyl produced a slight decrease in the body weight of the live fetuses at the high dose, which may be attributed to maternal toxicity. Under the conditions of the assay, there was no evidence for fentanyl induced adverse effects on embryo-fetal development at doses up to 0.4 mg/kg (approximately 3 times the daily human dose administered by a 100 mcg/hr patch on a mg/m^2 basis).

There are no adequate and well-controlled studies in pregnant women. Fentanyl transdermal system should be used during pregnancy only if the potential benefit justifies the potential risk to the fetus.

Nonteratogenic Effects

Chronic maternal treatment with fentanyl during pregnancy has been associated with transient respiratory depression, behavioral changes, or seizures characteristic of neonatal abstinence syndrome in newborn infants. Symptoms of neonatal respiratory or neurological depression were no more frequent than expected in most studies of infants born to women treated acutely during labor with intravenous or epidural fentanyl. Transient neonatal muscular rigidity has been observed in infants whose mothers were treated with intravenous fentanyl.

The potential effects of fentanyl on prenatal and postnatal development were examined in the rat model. Female Wistar rats were treated with 0, 0.025, 0.1, or 0.4 mg/kg/day fentanyl via intravenous infusion from day 6 of pregnancy through 3 weeks of lactation. Fentanyl treatment (0.4 mg/kg/day) significantly decreased body weight in male and female pups and also decreased survival in pups at day 4. Both the mid-dose and high-dose of fentanyl animals demonstrated alterations in some physical landmarks of development (delayed incisor eruption and eye opening) and transient behavioral development (decreased locomotor activity at day 28 which recovered by day 50). The mid-dose and the high-dose are 0.4 and 1.6 times the daily human dose administered by a 100 mcg/hr patch on a mg/m^2 basis.

Labor and Delivery

Fentanyl readily passes across the placenta to the fetus; therefore, fentanyl transdermal system is not recommended for analgesia during labor and delivery.

Nursing Mothers

Fentanyl is excreted in human milk; therefore, fentanyl transdermal system is not recommended for use in nursing women because of the possibility of effects in their infants.

Pediatric Use

The safety of fentanyl transdermal system was evaluated in three open-label trials in 291 pediatric patients with chronic pain, 2 years of age through 18 years of age. Starting doses of 25 mcg/h and higher were used by 181 patients who had been on prior daily opioid doses of at least 45 mg/day of oral morphine or an equianalgesic dose of another opioid. Initiation of fentanyl transdermal system therapy in pediatric patients taking less than 60 mg/day of oral morphine or an equianalgesic dose of another opioid has not been evaluated in controlled clinical trials. Approximately 90% of the total daily opioid requirement (fentanyl transdermal system plus rescue medication) was provided by fentanyl transdermal system.

Fentanyl transdermal system was not studied in children under 2 years of age.

Fentanyl transdermal system should be administered to children only if they are opioid-tolerant and 2 years of age or older (see DOSAGE AND ADMINISTRATION and BOX WARNING).

To guard against accidental ingestion by children, use caution when choosing the application site for fentanyl transdermal system (see DOSAGE AND ADMINISTRATION) and monitor adhesion of the system closely.

Geriatric Use

Data from intravenous studies with fentanyl suggest that the elderly patients may have reduced clearance and a prolonged half-life. Moreover elderly patients may be more sensitive to the active substance than younger patients. A study conducted with the patch in elderly patients demonstrated that fentanyl pharmacokinetics did not differ significantly from young adult subjects, although peak serum concentrations tended to be lower and mean half-life values were prolonged to approximately 34 hours.

Respiratory depression is the chief hazard in elderly or debilitated patients, usually following large initial doses in non-tolerant patients or when opioids are given in conjunction with other agents that depress respiration.

Fentanyl transdermal system should be used with caution in elderly, cachectic, or debilitated patients as they may have altered pharmacokinetics due to poor fat stores, muscle wasting or altered clearance (see DOSAGE AND ADMINISTRATION).

ADVERSE REACTIONS

In post-marketing experience, deaths from hypoventilation due to use of fentanyl transdermal system have been reported (see BOX WARNING and CONTRAINDICATIONS).

Pre-Marketing Clinical Trial Experience

Although fentanyl transdermal system use in post-operative or acute pain and in patients who are not opioid-tolerant is CONTRAINDICATED, the safety of fentanyl transdermal system was originally evaluated in 357 post-operative adult patients for 1 to 3 days and 153 cancer patients for a total of 510 patients. The duration of fentanyl transdermal system use varied in cancer patients; 56% of patients used fentanyl transdermal system for over 30 days, 28% continued treatment for more than 4 months, and 10% used fentanyl transdermal system for more than 1 year.

Hypoventilation was the most serious adverse reaction observed in 13 (4%) post-operative patients and in 3 (2%) of the cancer patients. Hypotension and hypertension were observed in 11 (3%) and 4 (1%) of the opioid-naive patients.

Various adverse events were reported; a causal relationship to fentanyl transdermal system was not always determined. The frequencies presented here reflect the actual frequency of each adverse effect in patients who received fentanyl transdermal system. There has been no attempt to correct for a placebo effect, concomitant use of other opioids, or to subtract the frequencies reported by placebo-treated patients in controlled trials.

Adverse reactions reported in 153 cancer patients at a frequency of 1% or greater are presented in Table 1; similar reactions were seen in the 357 post-operative patients.

In the pediatric population, the safety of fentanyl transdermal system has been evaluated in 291 patients with chronic pain 2–18 years of age. The duration of fentanyl transdermal system use varied; 20% of pediatric patients were treated for ≤ 15 days; 46% for 16–30 days; 16% for 31–60 days; and 17% for at least 61 days. Twenty-five patients were treated with fentanyl transdermal system for at least 4 months and 9 patients for more than 9 months.

There was no apparent pediatric-specific risk associated with fentanyl transdermal system use in children as young as 2 years old when used as directed. The most common adverse events were fever (35%), vomiting (33%), and nausea (24%).

Adverse events reported in pediatric patients at a rate of ≥1% are presented in Table 1.

TABLE 1: ADVERSE EVENTS (at rate of ≥ 1%) Adult (N=380) and Pediatric (N=291) Clinical Trial Experience
Body System | Adults | Pediatrics
Body as a Whole | Abdominal pain [Reactions occurring in 3% – 10% of fentanyl transdermal system patients] , headache, fatigue, back pain, fever, influenza-like symptoms, accidental injury, rigors | Pain, headache, fever, syncope, abdominal pain, allergic reaction, flushing
Cardiovascular | Arrhythmia, chest pain | Hypertension, tachycardia
Digestive | Nausea [Reactions occurring in 10% or more of fentanyl transdermal system patients] , vomiting, constipation, dry mouth, anorexia, diarrhea, dyspepsia, flatulence | Nausea, vomiting, constipation, dry mouth, diarrhea
Nervous | Somnolence, insomnia, confusion, asthenia, dizziness, nervousness, hallucinations, anxiety, depression, euphoria, tremor, abnormal coordination, speech disorder, abnormal thinking, abnormal gait, abnormal dreams, agitation, paresthesia, amnesia, syncope, paranoid reaction | Somnolence, nervousness, insomnia, asthenia, hallucinations, anxiety, depression, convulsions, dizziness, tremor, speech disorder, agitation, stupor, confusion, paranoid reaction
Respiratory | Dyspnea, hypoventilation, apnea, hemoptysis, pharyngitis, hiccups, bronchitis, rhinitis, sinusitis, upper respiratory tract infection | Dyspnea, respiratory depression, rhinitis, coughing
Skin and Appendages | Sweating, pruritus, rash, application site reaction – erythema, papules, itching, edema | Pruritus, application site reaction, sweating increased, rash, rash erythematous, skin reaction localized
Urogenital | Urinary retention, Micturition disorder | Urinary retention

The following adverse effects have been reported in less than 1% of the 510 adult post-operative and cancer patients studied:

Cardiovascular: bradycardia

Digestive: abdominal distention

Nervous: aphasia, hypertonia, vertigo, stupor, hypotonia, depersonalization, hostility

Respiratory: stertorous breathing, asthma, respiratory disorder

Skin and Appendages, General: exfoliative dermatitis, pustules

Special Senses: amblyopia

Urogenital: bladder pain, oliguria, urinary frequency

Post-Marketing Experience - Adults

The following adverse reactions have been reported in association with the use of fentanyl transdermal system and not reported in the pre-marketing adverse reactions section above:

Body as a Whole: edema

Cardiovascular: tachycardia

Metabolic and Nutritional: weight loss

Special Senses: blurred vision

Urogenital: decreased libido, anorgasmia, ejaculatory difficulty

DRUG ABUSE AND ADDICTION

Fentanyl transdermal system contains a high concentration of fentanyl, a potent Schedule II opioid agonist. Schedule II opioid substances, which include hydromorphone, methadone, morphine, oxycodone, and oxymorphone, have the highest potential for abuse and risk of fatal overdose due to respiratory depression. Fentanyl, like morphine and other opioids used in analgesia, can be abused and is subject to criminal diversion.

The high content of fentanyl in the patches (fentanyl transdermal system) may be a particular target for abuse and diversion.

Addiction is a primary, chronic, neurobiologic disease, with genetic, psychosocial, and environmental factors influencing its development and manifestations. It is characterized by behaviors that include one or more of the following: impaired control over drug use, compulsive use, continued use despite harm, and craving. Drug addiction is a treatable disease, utilizing a multidisciplinary approach, but relapse is common.

"Drug seeking" behavior is very common in addicts and drug abusers. Drug-seeking tactics include emergency calls or visits near the end of office hours, refusal to undergo appropriate examination, testing or referral, repeated "loss" of prescriptions, tampering with prescriptions and reluctance to provide prior medical records or contact information for other treating physician(s). "Doctor shopping" to obtain additional prescriptions is common among drug abusers and people suffering from untreated addiction.

Abuse and addiction are separate and distinct from physical dependence and tolerance. Physicians should be aware that addiction may be accompanied by concurrent tolerance and symptoms of physical dependence. In addition, abuse of opioids can occur in the absence of true addiction and is characterized by misuse for non-medical purposes, often in combination with other psychoactive substances. Since fentanyl transdermal system may be diverted for non-medical use, careful record keeping of prescribing information, including quantity, frequency, and renewal requests is strongly advised.

Proper assessment of the patient, proper prescribing practices, periodic re-evaluation of therapy, and proper dispensing and storage are appropriate measures that help to limit abuse of opioid drugs.

Fentanyl transdermal system patches are intended for transdermal use (to be applied on the skin) only. Do not use a fentanyl transdermal system patch if the pouch seal is broken or the patch is cut, damaged, or changed in any way.

OVERDOSAGE

Clinical Presentation

The manifestations of fentanyl overdosage are an extension of its pharmacologic actions with the most serious significant effect being hypoventilation.

Treatment

For the management of hypoventilation, immediate countermeasures include removing the fentanyl transdermal system system and physically or verbally stimulating the patient. These actions can be followed by administration of a specific narcotic antagonist such as naloxone. The duration of hypoventilation following an overdose may be longer than the effects of the narcotic antagonist's action (the half-life of naloxone ranges from 30 to 81 minutes). The interval between IV antagonist doses should be carefully chosen because of the possibility of re-narcotization after system removal; repeated administration of naloxone may be necessary. Reversal of the narcotic effect may result in acute onset of pain and the release of catecholamines.

Always ensure a patent airway is established and maintained, administer oxygen and assist or control respiration as indicated and use an oropharyngeal airway or endotracheal tube if necessary. Adequate body temperature and fluid intake should be maintained.

If severe or persistent hypotension occurs, the possibility of hypovolemia should be considered and managed with appropriate parenteral fluid therapy.

DOSAGE AND ADMINISTRATION

Special Precautions

Fentanyl transdermal system contains a high concentration of a potent Schedule II opioid agonist, fentanyl. Schedule II opioid substances which include fentanyl, hydromorphone, methadone, morphine, oxycodone, and oxymorphone have the highest potential for abuse and associated risk of fatal overdose due to respiratory depression. Fentanyl can be abused and is subject to criminal diversion. The high content of fentanyl in the patches (fentanyl transdermal system) may be a particular target for abuse and diversion.

Fentanyl transdermal system patches are intended for transdermal use (on intact skin) only. The fentanyl transdermal system patch should not be used if the pouch seal is broken, or the patch is cut, damaged, or changed in any way.

Each fentanyl transdermal system patch may be worn continuously for 72 hours. The next patch should be applied to a different skin site after removal of the previous transdermal system.

If problems with adhesion of the fentanyl transdermal system patch occur, the edges of the patch may be taped with first aid tape. If problems with adhesion persist, the patch may be overlayed with a transparent adhesive film dressing (e.g., Bioclusive™ or Tegaderm™).

If the patch falls off before 72 hours, dispose of it by folding in half and flushing down the toilet. A new patch may be applied to a different skin site.

Fentanyl transdermal system is ONLY for use in patients who are already tolerant to opioid therapy of comparable potency. Use in non-opioid tolerant patients may lead to fatal respiratory depression. Overestimating the fentanyl transdermal system dose when converting patients from another opioid medication can result in fatal overdose with the first dose. Due to the mean half-life of approximately 20‑27 hours, patients who are thought to have had a serious adverse event, including overdose, will require monitoring and treatment for at least 24 hours.

The concomitant use of fentanyl transdermal system with all cytochrome P450 3A4 inhibitors (such as ritonavir, ketoconazole, itraconazole, troleandomycin, clarithromycin, nelfinavir, nefazodone, amiodarone, amprenavir, aprepitant, diltiazem, erythromycin, fluconazole, fosamprenavir, grapefruit juice, and verapamil) may result in an increase in fentanyl plasma concentrations, which could increase or prolong adverse drug effects and may cause potentially fatal respiratory depression. Patients receiving fentanyl transdermal system and any CYP3A4 inhibitor should be carefully monitored for an extended period of time and dosage adjustments should be made if warranted (see BOX WARNING, CLINICAL PHARMACOLOGY – Drug Interactions, WARNINGS, and PRECAUTIONS for further information).

Pediatric patients converting to fentanyl transdermal system with a 25 mcg/h patch should be opioid-tolerant and receiving at least 60 mg of oral morphine or the equivalent per day. The dose conversion schedule described in Table C, and method of titration described below are recommended in opioid-tolerant pediatric patients over 2 years of age with chronic pain (see PRECAUTIONS – Pediatric Use).

Respiratory depression is the chief hazard in elderly or debilitated patients, usually following large initial doses in non-tolerant patients, or when opioids are given in conjunction with other agents that depress respiration.

Fentanyl transdermal system should be used with caution in elderly, cachectic, or debilitated patients as they may have altered pharmacokinetics due to poor fat stores, muscle wasting, or altered clearance (see CLINICAL PHARMACOLOGY – Special Populations, Geriatric Use).

General Principles

Fentanyl transdermal system is indicated for management of persistent, moderate to severe chronic pain that:

- requires continuous, around-the-clock opioid administration for an extended period of time
- cannot be managed by other means such as non-steroidal analgesics, opioid combination products, or immediate-release opioids.

Fentanyl transdermal system should ONLY be used in patients who are already receiving opioid therapy, who have demonstrated opioid tolerance, and who require a total daily dose at least equivalent to fentanyl transdermal system 25 mcg/h. Patients who are considered opioid-tolerant are those who have been taking, for a week or longer, at least 60 mg of morphine daily, or at least 30 mg of oral oxycodone daily, or at least 8 mg oral hydromorphone daily, or an equianalgesic dose of another opioid.

Because serious or life-threatening hypoventilation could occur, fentanyl transdermal system is contraindicated:

- in patients who are not opioid-tolerant
- in the management of acute pain or in patients who require opioid analgesia for a short period of time.
- in the management of post-operative pain, including use after out-patient or day surgeries (e.g., tonsillectomies)
- in the management of mild pain
- in the management of intermittent pain (e.g., use on an as needed basis [prn])

(See CONTRAINDICATIONS for further information.)

Safety of fentanyl transdermal system has not been established in children under 2 years of age. fentanyl transdermal system should be administered to children only if they are opioid-tolerant and 2 years of age or older (see PRECAUTIONS - Pediatric Use).

Prescribers should individualize treatment using a progressive plan of pain management such as outlined by the World Health Organization, the Agency for Health Research and Quality, the Federation of State Medical Boards Model Policy, or the American Pain Society.

With all opioids, the safety of patients using the products is dependent on health care practitioners prescribing them in strict conformity with their approved labeling with respect to patient selection, dosing, and proper conditions for use.

As with all opioids, dosage should be individualized. The most important factor to be considered in determining the appropriate dose is the extent of pre-existing opioid-tolerance (see BOX WARNING and CONTRAINDICATIONS). Initial doses should be reduced in elderly or debilitated patients (see PRECAUTIONS).

Fentanyl transdermal system should be applied to intact, non-irritated, and non-irradiated skin on a flat surface such as the chest, back, flank, or upper arm. In young children and persons with cognitive impairment, adhesion should be monitored and the upper back is the preferred location to minimize the potential of inappropriate patch removal. Hair at the application site should be clipped (not shaved) prior to system application. If the site of fentanyl transdermal system application must be cleansed prior to application of the patch, do so with clear water. Do not use soaps, oils, lotions, alcohol, or any other agents that might irritate the skin or alter its characteristics. Allow the skin to dry completely prior to patch application.

Fentanyl transdermal system should be applied immediately upon removal from the sealed package. Do not use if the pouch seal is broken. Do not alter the patch (e.g., cut) in any way prior to application and do not use cut or damaged patches.

The transdermal system should be pressed firmly in place with the palm of the hand for 30 seconds, making sure the contact is complete, especially around the edges.

Fentanyl transdermal system should be kept out of the reach of children. Used patches should be folded so that the adhesive side of the patch adheres to itself, then the patch should be flushed down the toilet immediately upon removal. Patients should dispose of any patches remaining from a prescription as soon as they are no longer needed. Unused patches should be removed from their pouches, folded so that the adhesive side of the patch adheres to itself, and flushed down the toilet.

Dose Selection

Doses must be individualized based upon the status of each patient and should be assessed at regular intervals after fentanyl transdermal system application. Reduced doses of fentanyl transdermal system are suggested for the elderly and other groups discussed in PRECAUTIONS.

Fentanyl transdermal system is ONLY for use in patients who are already tolerant to opioid therapy of comparable potency. Use in non-opioid tolerant patients may lead to fatal respiratory depression.

In selecting an initial fentanyl transdermal system dose, attention should be given to 1) the daily dose, potency, and characteristics of the opioid the patient has been taking previously (e.g., whether it is a pure agonist or mixed agonist-antagonist), 2) the reliability of the relative potency estimates used to calculate the fentanyl transdermal system dose needed (potency estimates may vary with the route of administration), 3) the degree of opioid tolerance and 4) the general condition and medical status of the patient. Each patient should be maintained at the lowest dose providing acceptable pain control.

Initial Fentanyl Transdermal System Dose Selection

Overestimating the fentanyl transdermal system dose when converting patients from another opioid medication can result in fatal overdose with the first dose. Due to the mean half-life of approximately 20‑27 hours, patients who are thought to have had a serious adverse event, including overdose, will require monitoring and treatment for at least 24 hours.

There has been no systematic evaluation of fentanyl transdermal system as an initial opioid analgesic in the management of chronic pain, since most patients in the clinical trials were converted to fentanyl transdermal system from other narcotics. The efficacy of fentanyl transdermal system 12 mcg/h as an initiating dose has not been determined. In addition, patients who are not opioid-tolerant have experienced hypoventilation and death during use of fentanyl transdermal system. Therefore, fentanyl transdermal system should be used only in patients who are opioid-tolerant.

To convert adult and pediatric patients from oral or parenteral opioids to fentanyl transdermal system, use Table C:

Alternatively, for adult and pediatric patients taking opioids or doses not listed in Table C, use the following methodology:

1. Calculate the previous 24-hour analgesic requirement.
2. Convert this amount to the equianalgesic oral morphine dose using Table D.
3. Table E displays the range of 24-hour oral morphine doses that are recommended for conversion to each fentanyl transdermal system dose. Use this table to find the calculated 24-hour morphine dose and the corresponding fentanyl transdermal system dose. Initiate fentanyl transdermal system treatment using the recommended dose and titrate patients upwards (no more frequently than every 3 days after the initial dose or than every 6 days thereafter) until analgesic efficacy is attained. The recommended starting dose when converting from other opioids to fentanyl transdermal system is likely too low for 50% of patients. This starting dose is recommended to minimize the potential for overdosing patients with the first dose. For delivery rates in excess of 100 mcg/h, multiple systems may be used.

TABLE C [Table C should not be used to convert from fentanyl transdermal system to other therapies because this conversion to fentanyl transdermal system is conservative. Use of table C for conversion to other analgesic therapies can overestimate the dose of the new agent. Overdosage of the new analgesic agent is possible (see DOSAGE AND ADMINISTRATION - Discontinuation of Fentanyl Transdermal System).] : DOSE CONVERSION GUIDELINES
Current Analgesic | Daily Dosage (mg/d)
Oral morphine | 60–134 | 135–224 | 225–314 | 315–404
IM/IV morphine | 10–22 | 23–37 | 38–52 | 53–67
Oral oxycodone | 30–67 | 67.5–112 | 112.5–157 | 157.5–202
IM/IV oxycodone | 15–33 | 33.1–56 | 56.1–78 | 78.1–101
Oral codeine | 150–447 | 448–747 | 748–1047 | 1048–1347
Oral hydromorphone | 8–17 | 17.1–28 | 28.1–39 | 39.1–51
IV hydromorphone | 1.5–3.4 | 3.5–5.6 | 5.7–7.9 | 8–10
IM meperidine | 75–165 | 166–278 | 279–390 | 391–503
Oral methadone | 20–44 | 45–74 | 75–104 | 105–134
IM methadone | 10–22 | 23–37 | 38–52 | 53–67
Recommended Fentanyl Transdermal System Dose | 25 mcg/h | 50 mcg/h | 75 mcg/h | 100 mcg/h
Alternatively, for adult and pediatric patients taking opioids or doses not listed in Table C, use the conversion methodology outlined above with Table D.

TABLE D [Table D should not be used to convert from fentanyl transdermal system to other therapies because this conversion to fentanyl transdermal system is conservative. Use of Table D for conversion to other analgesic therapies can overestimate the dose of the new agent. Overdosage of the new analgesic agent is possible (see Dosage And Administration - Discontinuation of Fentanyl Transdermal System).] [All IM and PO doses in this chart are considered equivalent to 10 mg of IM morphine in analgesic effect. IM denotes intramuscular, PO oral, and PR rectal.] : EQUIANALGESIC POTENCY CONVERSION
Name | Equianalgesic Dose (mg)
Name | IM [Based on single-dose studies in which an intramuscular dose of each drug listed was compared with morphine to establish the relative potency. Oral doses are those recommended when changing from parenteral to an oral route. Reference: Foley, K.M. (1985) The treatment of cancer pain. NEJM 313(2):84–95.] , [Although controlled studies are not available, in clinical practice it is customary to consider the doses of opioid given IM, IV, or subcutaneously to be equivalent. There may be some differences in pharmacokinetic parameters such as Cmax and Tmax.] | PO
Morphine | 10 | 60 (30) [The conversion ratio of 10 mg parenteral morphine = 30 mg oral morphine is based on clinical experience in patients with chronic pain. The conversion ratio of 10 mg parenteral morphine = 60 mg oral morphine is based on a potency study in acute pain. Reference: Ashburn and Lipman (1993) Management of pain in the cancer patient. Anesth Analg 76:402–416.]
Hydromorphone (Dilaudid®) | 1.5 | 7.5
Methadone (Dolophine®) | 10 | 20
Oxycodone | 15 | 30
Levorphanol (Levo-Dromoran®) | 2 | 4
Oxymorphone (Numorphan®) | 1 | 10 (PR)
Meperidine (Demerol®) | 75 | —
Codeine | 130 | 200

TABLE E [Table E should not be used to convert from fentanyl transdermal system to other therapies because this conversion to fentanyl transdermal system is conservative. Use of Table E for conversion to other analgesic therapies can overestimate the dose of the new agent. Overdosage of the new analgesic agent is possible (see DOSAGE AND ADMINISTRATION - Discontinuation of Fentanyl Transdermal System).] : RECOMMENDED INITIAL FENTANYL TRANSDERMAL SYSTEM DOSE BASED UPON DAILY ORAL MORPHINE DOSE
Oral 24-hour Morphine (mg/day) | Fentanyl transdermal system Dose (mcg/h)
60–134 | 25
135–224 | 50
225–314 | 75
315–404 | 100
405–494 | 125
495–584 | 150
585–674 | 175
675–764 | 200
765–854 | 225
855–944 | 250
945–1034 | 275
1035–1124 | 300
NOTE: In clinical trials, these ranges of daily oral morphine doses were used as a basis for conversion to fentanyl transdermal system.

The majority of patients are adequately maintained with fentanyl transdermal system administered every 72 hours. Some patients may not achieve adequate analgesia using this dosing interval and may require systems to be applied every 48 hours rather than every 72 hours. An increase in the fentanyl transdermal system dose should be evaluated before changing dosing intervals in order to maintain patients on a 72-hour regimen. Dosing intervals less than every 72 hours were not studied in children and adolescents and are not recommended.

Because of the increase in serum fentanyl concentration over the first 24 hours following initial system application, the initial evaluation of the maximum analgesic effect of fentanyl transdermal system cannot be made before 24 hours of wearing. The initial fentanyl transdermal system dose may be increased after 3 days (see DOSAGE AND ADMINISTRATION - Dose Titration).

During the initial application of fentanyl transdermal system, patients should use short-acting analgesics as needed until analgesic efficacy with fentanyl transdermal system is attained. Thereafter, some patients still may require periodic supplemental doses of other short-acting analgesics for "breakthrough" pain.

Dose Titration

The recommended initial fentanyl transdermal system dose based upon the daily oral morphine dose is conservative, and 50% of patients are likely to require a dose increase after initial application of fentanyl transdermal system. The initial fentanyl transdermal system dose may be increased after 3 days based on the daily dose of supplemental opioid analgesics required by the patient in the second or third day of the initial application.

Physicians are advised that it may take up to 6 days after increasing the dose of fentanyl transdermal system for the patient to reach equilibrium on the new dose (see graph in CLINICAL PHARMACOLOGY). Therefore, patients should wear a higher dose through two applications before any further increase in dosage is made on the basis of the average daily use of a supplemental analgesic.

Appropriate dosage increments should be based on the daily dose of supplementary opioids, using the ratio of 45 mg/24 hours of oral morphine to a 12.5 mcg/h increase in fentanyl transdermal system dose. Fentanyl transdermal system -12 delivers 12.5 mcg/h of fentanyl.

Discontinuation of FENTANYL TRANSDERMAL SYSTEM

To convert patients to another opioid, remove fentanyl transdermal system and titrate the dose of the new analgesic based upon the patient's report of pain until adequate analgesia has been attained. Upon system removal, 17 hours or more are required for a 50% decrease in serum fentanyl concentrations. Opioid withdrawal symptoms (such as nausea, vomiting, diarrhea, anxiety, and shivering) are possible in some patients after conversion or dose adjustment. For patients requiring discontinuation of opioids, a gradual downward titration is recommended since it is not known at what dose level the opioid may be discontinued without producing the signs and symptoms of abrupt withdrawal.

Tables C, D, and E should not be used to convert from fentanyl transdermal system to other therapies. Because the conversion to fentanyl transdermal system is conservative, use of Tables C, D, and E for conversion to other analgesic therapies can overestimate the dose of the new agent. Overdosage of the new analgesic agent is possible.

HOW SUPPLIED

Fentanyl transdermal system is supplied in cartons containing 5 individually packaged systems. See chart for information regarding individual systems.

Fentanyl Transdermal System Dose (mcg/h) | System Size (cm^2) | Fentanyl Content (mg) | NDC Number
Fentanyl transdermal system-12 | 5.25 | 2.1 | 0781-7240-55
Fentanyl transderml system-25 | 10.5 | 4.2 | 0781-7241-55
Fentanyl transdermal system-50 | 21 | 8.4 | 0781-7242-55
Fentanyl transdermal system-75 | 31.5 | 12.6 | 0781-7243-55
Fentanyl transdermal system-100 | 42 | 16.8 | 0781-7244-55

Safety and Handling

Fentanyl transdermal system is supplied in sealed transdermal systems which pose little risk of exposure to health care workers. Do not use a fentanyl transdermal system patch if the pouch seal is broken or the patch is cut, damaged, or changed in any way.

KEEP FENTANYL TRANSDERMAL SYSTEM OUT OF THE REACH OF CHILDREN AND PETS.

Store in original unopened pouch. Store up to 25°C (77°F); excursions permitted to 15 – 30°C (59 – 86°F). Apply immediately after removal from individually sealed pouch. Do not use if the pouch seal is broken. For transdermal use only.

Bioclusive™ is a trademark of Ethicon, Inc.
Tegaderm™ is a trademark of 3M

A schedule CII narcotic. DEA order form required.

Manufactured by:
ALZA Corporation
Vacaville, CA 95688 for

Sandoz Inc. Broomfield, CO 80020

Revised July 2009

Insert new code

MEDICATION GUIDE

FENTANYL TRANSDERMAL SYSTEM CII

IMPORTANT:

- Keep fentanyl transdermal system in a safe place away from children and pets. Accidental use by a child or pet is a medical emergency and may result in death. If a child or pet accidentally uses fentanyl transdermal system, get emergency help right away.
- Make sure you read the separate "Instructions for Applying a Fentanyl Transdermal System Patch." Always use a fentanyl transdermal system patch the right way. Fentanyl transdermal system can cause serious breathing problems and death, especially if it is used the wrong way.
- Fentanyl transdermal system is a federally controlled substance (C-II) because it can be abused. Keep fentanyl transdermal system in a safe place to prevent theft. Selling or giving away fentanyl transdermal system may harm others, and is against the law.
- Tell your doctor if you (or a family member) have ever abused or been dependent on alcohol, prescription medicines or street drugs.

Read the Medication Guide that comes with fentanyl transdermal system before you start using it and each time you get a new prescription. There may be new information. This Medication Guide does not take the place of talking to your healthcare provider about your medical condition or your treatment. Make sure you read and understand all the instructions for using fentanyl transdermal system. Do not use fentanyl transdermal system unless you understand everything. Talk to your healthcare provider if you have questions.

What is the most important information I should know about fentanyl transdermal system?

Fentanyl transdermal system is a skin patch that contains fentanyl. Fentanyl is a very strong opioid narcotic pain medicine that can cause serious and life-threatening breathing problems. Serious and life-threatening breathing problems can happen because of an overdose or if the dose you are using is too high for you. Call your doctor right away or get emergency medical help if you:

- have trouble breathing, or have slow or shallow breathing
- have a slow heartbeat
- have severe sleepiness
- have cold, clammy skin
- feel faint, dizzy, confused, or cannot think, walk, or talk normally
- have a seizure
- have hallucinations

Fentanyl transdermal system is only for adults and children over the age of two with persistent, moderate to severe chronic pain and who:

- are already using another strong opioid narcotic pain medicine around-the-clock, and have been using the medicine regularly for a week or longer. This is called being opioid-tolerant.
- have pain that cannot be controlled with other medicines

Do not use fentanyl transdermal system:

- if you are not already using another opioid narcotic medicine and are not opioid tolerant
- if you need opioid pain medicines for only a short time
- for pain from surgery, medical or dental procedures
- if your pain can be taken care of by occasional use of other pain medicines
- in children who are less than 2 years of age
- if you have asthma symptoms or have severe asthma

A fentanyl transdermal system patch must be used only on the skin of the person for whom it was prescribed. If the patch comes off and accidentally sticks to the skin of another person, take the patch off of that person right away, wash the area with water, and get medical care for them right away.

Fentanyl transdermal system patch is not safe for everyone. Tell your doctor about all of your medical conditions.

Tell your doctor if you are planning to become pregnant, are pregnant, or breastfeeding. Fentanyl transdermal system may cause serious harm to a baby.

Tell your doctor about all the medicines you take. Some medicines may cause serious or life-threatening side effects when used with fentanyl transdermal system. Your doctor will tell you if it is safe to take other medicines while you are using fentanyl transdermal system.

Know the medicines you take. Keep a list of your medicines to show to your doctor and pharmacist.

How should I use fentanyl transdermal system?

Read the separate "Instructions for Applying a Fentanyl Transdermal System Patch".

- You must always use fentanyl transdermal system patches the right way:
  - Do not use a fentanyl transdermal system patch if the pouch seal is broken, or the patch is cut, damaged, or changed in any way.
  - Do not use heat sources such as heating pads, electric blankets, heat lamps, tanning lamps, saunas, hot tubs, or heated waterbeds while wearing a fentanyl transdermal system patch.
  - Do not take hot baths or sunbathe while wearing a fentanyl transdermal system patch.
- If you have problems with the fentanyl transdermal system patch not sticking:
  1. Apply first aid tape only to the edges of the patch.
  2. If problems with the patch not sticking persist, cover the patch with Bioclusive™ or Tegaderm™. These are special see-through adhesive dressings. Never cover a fentanyl transdermal system patch with any other bandage or tape.
- If your fentanyl transdermal system patch falls off before 3 days or 72 hours, fold the sticky side together and flush down a toilet. Put a new one on at a different skin site.
- Do not change your dose unless your doctor tells you to. Your doctor may change your dose after seeing how the medicine affects you. Do not use fentanyl transdermal system more often than prescribed. Call your doctor if your pain is not well controlled while using fentanyl transdermal system.
- Do not stop using fentanyl transdermal system suddenly. Stopping fentanyl transdermal system suddenly can make you sick with withdrawal symptoms (for example, nausea, vomiting, diarrhea, anxiety, and shivering). Your body can develop a physical dependence on fentanyl transdermal system. If your doctor decides you no longer need fentanyl transdermal system, ask how to slowly reduce this medicine so you don't have withdrawal symptoms. Do not stop taking fentanyl transdermal system without talking to your doctor.
- Do not wear more than one fentanyl transdermal system patch at a time, unless your doctor tells you to do so.
- Call your doctor right away if
  - You get a fever higher than 102°F
  - Your body temperature increases from exercise
    A fever or increase in body temperature may cause too much of the medicine in fentanyl transdermal system to pass into your body.
- If you use more fentanyl transdermal system than your doctor has prescribed, get emergency medical help right away.
- Do not drink any alcohol while using fentanyl transdermal system. Alcohol can increase your chances of having serious side effects.
- Do not drive, operate heavy machinery, or do other possibly dangerous activities until you know how fentanyl transdermal system affects you. Fentanyl transdermal system can make you sleepy. Ask your doctor to tell you when it is okay to do these activities.
- When you remove your fentanyl transdermal system patch, fold the sticky sides of a used fentanyl transdermal system patch together and flush it down the toilet. Do not put used fentanyl transdermal system patches in a trash can.

What are the possible side effects of fentanyl transdermal system?

Serious side effects include:

- Life-threatening breathing problems. See "What is the most important information I should know about fentanyl transdermal system?"
- Low blood pressure. This can make you feel dizzy if you get up too fast from sitting or lying down.

The common side effects with fentanyl transdermal system are nausea, vomiting, constipation, dry mouth, sleepiness, confusion, weakness, sweating, and pain and redness where the patch was applied.

Constipation is a very common side effect of all opioid medicines. Talk to your doctor about the use of laxatives and stool softeners to prevent or treat constipation while taking fentanyl transdermal system.

Talk to your doctor about any side effect that concerns you.

These are not all the possible side effects of fentanyl transdermal system. For a complete list, ask your doctor or pharmacist.

Call your doctor for medical advice about side effects. You may report side effects to FDA at 1-800-FDA-1088.

How should I store fentanyl transdermal system?

- Store in original unopened pouch at room temperature.
- Keep a fentanyl transdermal system patch in its protective pouch until you are ready to use it.
- Keep fentanyl transdermal system in a safe place out of the reach of children and pets.
- Dispose of fentanyl transdermal system patches you no longer need. Open the unused packages, fold the sticky sides of the patches together, and flush them down the toilet.

General information about the safe and effective use of fentanyl transdermal system

- Do not use fentanyl transdermal system for a condition for which it was not prescribed.
- Do not give fentanyl transdermal system to other people, even if they have the same symptoms you have. Fentanyl transdermal system can harm other people and even cause death. Sharing fentanyl transdermal system is against the law.

This Medication Guide summarizes the most important information about fentanyl transdermal system. If you would like more information, talk with your doctor. You can ask your doctor or pharmacist for information about fentanyl transdermal system that is written for doctors.

For questions about the Sandoz fentanyl transdermal system, call the Sandoz Customer Relations Center at 1-800-525-8747. If this is a medical emergency, please call 911.

What are the ingredients of fentanyl transdermal system?

Active Ingredient: fentanyl
Inactive ingredients: polyester/ethyl vinyl acetate film backing, polyacrylate adhesive.

This Medication Guide has been approved by the United States Food and Drug Administration.

Bioclusive™ is a trademark of Ethicon, Inc.
Tegaderm™ is a trademark of 3M

Manufactured by:
ALZA Corporation
Vacaville, CA 95688 for

Sandoz Inc., Broomfield, CO 80020

Insert new code

July 2009

PATIENT INFORMATION

FENTANYL TRANSDERMAL SYSTEM CII

Instructions for Applying a Fentanyl Transdermal System Patch

BEFORE APPLYING FENTANYL TRANSDERMAL SYSTEM

- Each fentanyl transdermal system patch is sealed in its own protective pouch. Do not remove a fentanyl transdermal system patch from the pouch until you are ready to use it.
- Do not use a fentanyl transdermal system patch if the seal is broken or the patch is cut, damaged or changed in any way.
- Fentanyl transdermal system patches are available in 5 different doses and patch sizes. Make sure you have the right dose patch or patches that have been prescribed for you.

APPLYING A FENTANYL TRANSDERMAL SYSTEM PATCH

1. Skin Areas Where the Fentanyl Transdermal System Patch May Be Applied:
  For adults:
  - Put the patch on the chest, back, flank (sides of the waist), or upper arm in a place where there is no hair (see Figures 1–4).
For children (and adults with mental impairment):
  - Put the patch on the upper back (see Figure 2). This will lower the chances that the child will remove the patch and put it in their mouth.
For adults and children
  - Do not put a fentanyl transdermal system patch on skin that is very oily, burned, broken out, cut, irritated, or damaged in any way.
  - Avoid sensitive areas or those that move around a lot. If there is hair, do not shave (shaving irritates the skin). Instead, clip hair as close to the skin as possible (see Figure 5).
  - Talk to your doctor if you have questions about skin application sites.

Figure 1
Figure 2
Figure 3
Figure 4
Figure 5

2. Prepare to Apply a Fentanyl Transdermal System Patch:
  - Choose the time of day that is best for you to apply fentanyl transdermal system. Change it at about the same time of day (3 days or 72 hours after you apply the patch) or as directed by your doctor.
  - Do not wear more than one fentanyl transdermal system patch at a time unless your doctor tells you to do so. Before putting on a new fentanyl transdermal system patch, remove the patch you have been wearing.
  - Clean the skin area with clear water only. Pat skin completely dry. Do not use anything on the skin such as soaps, lotions, oils, or alcohol before the patch is applied.

3. Open the Pouch: Fold and tear at slit, or cut at slit taking care so as not to cut the patch, and remove the fentanyl transdermal system patch. Each fentanyl transdermal system patch is sealed in its own protective pouch. Do not remove the fentanyl transdermal system patch from the pouch until you are ready to use it (see Figure 6).

Figure 6

4. Peel: Peel off both parts of the protective liner from the patch. Each fentanyl transdermal system patch has a clear plastic backing that can be peeled off in two pieces. This covers the sticky side of the patch. Carefully peel this backing off. Throw the clear plastic backing away. Touch the sticky side of the fentanyl transdermal system patch as little as possible (see Figure 7).

Figure 7

5. Press: Press the patch onto the chosen skin site with the palm of your hand and hold there for at least 30 seconds (see Figure 8). Make sure it sticks well, especially at the edges.
  - Fentanyl transdermal system may not stick to all patients. You need to check the patches often to make sure that they are sticking well to the skin.
  - If the patch falls off right away after applying, throw it away and put a new one on at a different skin site (see Disposing a Fentanyl Transdermal System Patch).
  - If you have a problem with the patch not sticking
    - Apply first aid tape only to the edges of the patch.
    - If you continue to have problems with the patch sticking, you may cover the patch with Bioclusive™ or Tegaderm™. These are special see-through adhesive dressings. Never cover a fentanyl transdermal system patch with any other bandage or tape. Remove the backing from the Bioclusive™ or Tegaderm™ dressing and place it carefully over the fentanyl transdermal system patch, smoothing it over the patch and your skin.
  - If your patch falls off later, but before 3 days (72 hours) of use, discard it properly (see Disposing a Fentanyl Transdermal System patch) and put a new one on at a different skin site. Be sure to let your doctor know that this has happened, and do not replace the new patch until 3 days (72 hours) after you put it on (or as directed by your doctor).

Figure 8

6. Wash your hands when you have finished applying a fentanyl transdermal system patch.

7. Remove a fentanyl transdermal system patch after wearing it for 3 days (72 hours) (see "Disposing a Fentanyl Transdermal System Patch"). Choose a different place on the skin to apply a new fentanyl transdermal system patch and repeat Steps 2 through 6.
  Do not apply the new patch to the same place as the last one.

Water and Fentanyl Transdermal System

- You can bathe, swim or shower while you are wearing a fentanyl transdermal system patch. If the patch falls off before 3 days (72 hours) after application, discard it properly (see Disposing a Fentanyl Transdermal System Patch) and put a new one on at a different skin site. Be sure to let your doctor know that this has happened, and do not replace the new patch until 3 days (72 hours) after you put it on (or as directed by your doctor).

Disposing a Fentanyl Transdermal System Patch

- Fold the used fentanyl transdermal system patch in half so that the sticky side sticks to itself (Figure 9). Flush the used fentanyl transdermal system down the toilet right away (Figure 10). A used fentanyl transdermal system patch CAN be VERY dangerous for or even lead to death in babies, children, pets, and adults who have not been prescribed fentanyl transdermal system.
- Throw away any fentanyl transdermal system patches that are left over from your prescription as soon as they are no longer needed. Remove the leftover patches from their protective pouch and remove the protective liner. Fold the patches in half with the sticky sides together, and flush the patches down the toilet. Do not flush the pouch or the protective liner down the toilet. These items can be thrown away in a trashcan.

Figure 9
Figure 10

Bioclusive™ is a trademark of Ethicon, Inc.

Tegaderm™ is a trademark of 3M

Rx Only

Manufactured by:
ALZA Corporation
Vacaville, CA 95688 for

Sandoz Inc., Broomfield, CO 80020

July 2009
Insert new code

PRINCIPAL DISPLAY PANEL

NDC 68258-3040-01------ALZA

12 mcg/h
Five (12 mcg/h) Systems
Fentanyl Transdermal System
12 mcg/h
CII
In vivo delivery of 12 mcg/h fentanyl for 72 hours
Because it can cause trouble breathing which can be fatal,
DO NOT USE fentanyl Transdermal System:
* For short term or any post-operative pain, or occasional pain
* For mild pain or pain that can be treated with non-opioid or as-needed opioid medication
* Unless you have been using other narcotic opioid medicines (must be opioid tolerant)
Each transdermal system contains: 2.1 mg fentanyl
DO NOT USE IF SEAL ON POUCH IS BROKEN
KEEP OUT OF REACH OF CHILDREN
Read enclosed Fentanyl Transdermal System
Medication Guide for important safety information.
Rx only
SANDOZ
ONLY
for pain requiring opioid medicine around-the-clock